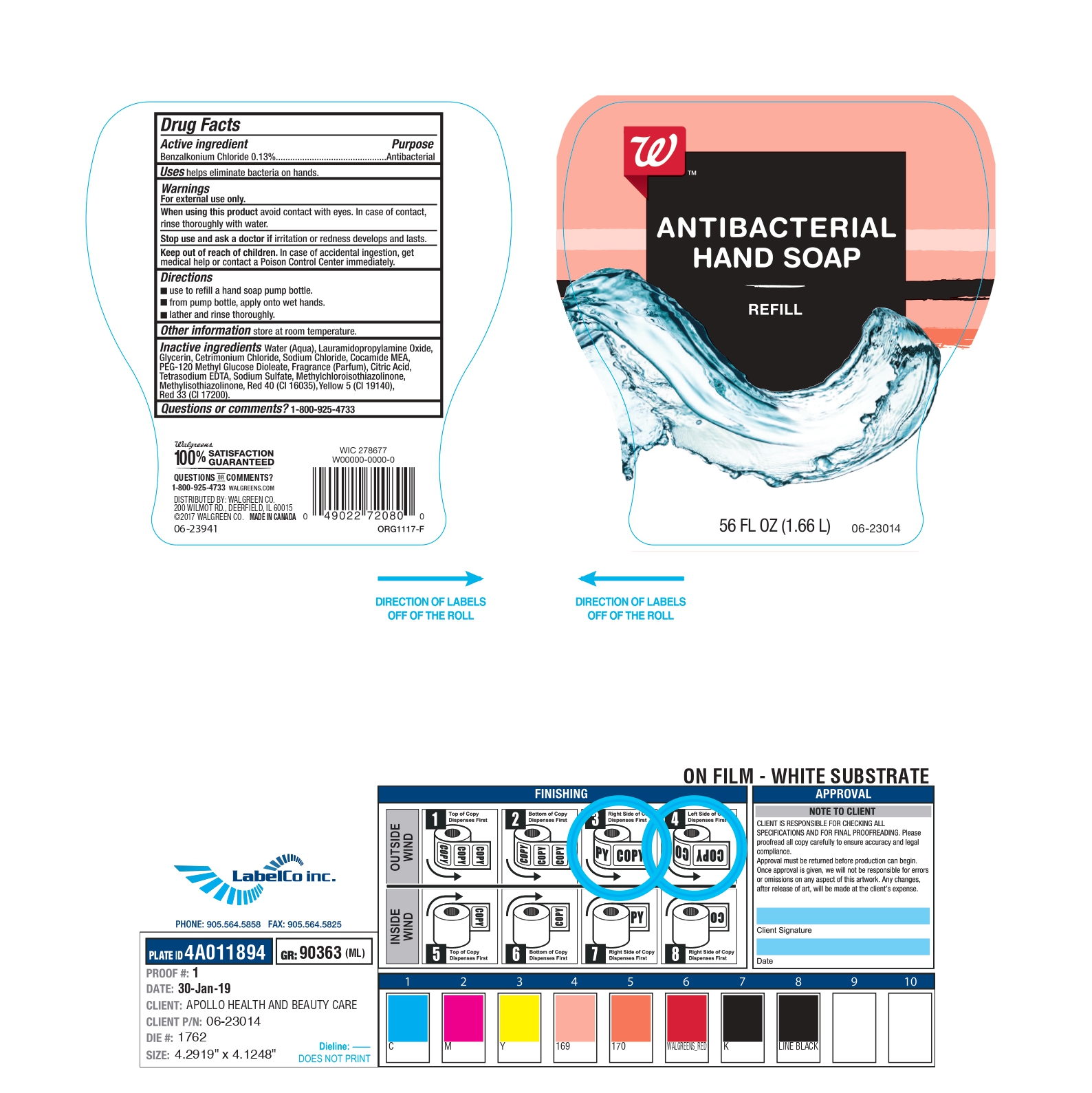 DRUG LABEL: Fresh Water
NDC: 79147-022 | Form: SOAP
Manufacturer: Spa Dent Inc
Category: otc | Type: HUMAN OTC DRUG LABEL
Date: 20210723

ACTIVE INGREDIENTS: BENZALKONIUM CHLORIDE 130 mg/100 mL
INACTIVE INGREDIENTS: WATER; LAURAMIDOPROPYLAMINE OXIDE; GLYCERIN; CETRIMONIUM CHLORIDE; SODIUM CHLORIDE; COCO MONOETHANOLAMIDE; PEG-120 METHYL GLUCOSE DIOLEATE; FRAGRANCE CLEAN ORC0600327; CITRIC ACID MONOHYDRATE; EDETATE SODIUM; SODIUM SULFATE; METHYLCHLOROISOTHIAZOLINONE; METHYLISOTHIAZOLINONE; FD&C RED NO. 40; FD&C YELLOW NO. 5; D&C RED NO. 33

Drug Facts

Active Ingredient.

Benzalkonium Chloride (0.13%)

Purpose

Antibacterial

Uses

Helps eliminate bacteria on hands

Warnings

For external use only

When using this product

Avoid contact with eyes. In case of contact, rinse thoroughly with water.

Stop use and ask a doctor.

If irritation or redness develops and lasts

Keep out of reach of children.

In case of accidental ingestion, get medical help or contact a Poison Control Center immediately.

Directions

- use to refill a hand soap pump bottle.
- From pump bottle, apply onto wet hands.
- Lather and rinse thoroughly.

Other Information

Store at room temperature

Inactive Ingredients

Water (Aqua), Lauramidopropylamine Oxide, Glycerin, Cetrimonium Chloride, Sodium Chloride, Cocamide MEA, PEG-120 Methyl Glucose Dioleate, Fragrance (Parfum), Citric Acid, Tetrasodium EDTA, Sodium Sulfate, Methylchloroisothiazolinone, Methylisothiazolinone, Red 40 (Cl 16035), Yellow 5 (Cl 19140), Red 33 (Cl 17200).

Questions or comments ?

1-800-925-4733